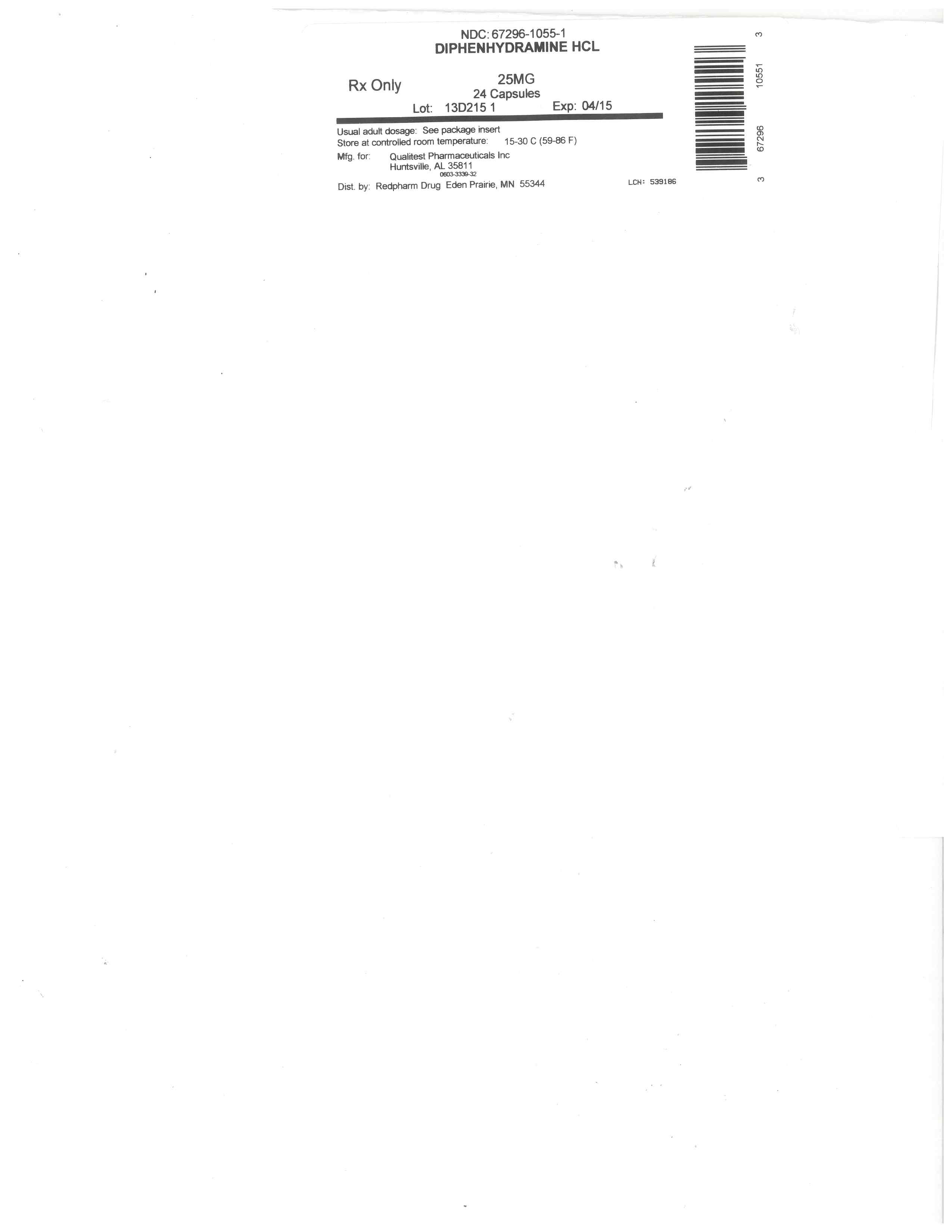 DRUG LABEL: Diphenhydramine Hydrochloride
NDC: 67296-1055 | Form: CAPSULE
Manufacturer: RedPharm Drug, Inc.
Category: otc | Type: HUMAN OTC DRUG LABEL
Date: 20200120

ACTIVE INGREDIENTS: DIPHENHYDRAMINE HYDROCHLORIDE 25 mg/1 1
INACTIVE INGREDIENTS: MAGNESIUM STEARATE; PROPYLPARABEN; FD&C BLUE NO. 1; GELATIN; LACTOSE, UNSPECIFIED FORM; POLYSORBATE 80; BENZYL ALCOHOL; BUTYLPARABEN; D&C RED NO. 28; FD&C RED NO. 40; METHYLPARABEN; SODIUM LAURYL SULFATE

diphenhydramine

DRUG FACTS

.

ACTIVE INGREDIENT

(in each capsule)

Diphenhydramine HCl 25 mg

PURPOSE

Antihistamine

INDICATIONS & USAGE

temporarily relieves these symptoms of hay fever or other upper respiratory allergies:

runny nose
itchy nose or throat
sneezing
itchy, watery eyes

WARNINGS

Do not use with any other product containing diphenhydramine, even one used on skin

Ask a doctor before use if you have

glaucoma
trouble urinating due to an enlarged prostate gland
a breathing problem such as emphysema or chronic bronchitis

Ask a doctor or pharmacist before use if you are taking sedatives or tranquilizers

When using this product

you may get very drowsy
avoid alcoholic drinks
alcohol, sedatives & tranquilizers may increase drowsiness
be careful when driving a motor vehicle or operating machinery
excitability may occur, especially in children

If pregnant or breast-feeding, ask a health professional before use.

KEEP OUT OF REACH OF CHILDREN.

In case of overdose, get medical help or contact a Poison Control Center right away.

DIRECTIONS

adults and children 12 years and over: take 1 to 2 capsules every 4-6 hours; not more than 6 doses in 24 hours
children under 12 years: ask a doctor

OTHER INFORMATION

store at 15-30 °C (59-86 °F)
protect from moisture
For 1000 Count: This is a bulk package. Dispense contents in a tight, light-resistant container with a child-resistant closure as defined in the USP

INACTIVE INGREDIENTS

benzyl alcohol, butylparaben, D&C red# 28, edible black ink, FD&C bule #1, FD&C red# 40, gelatin, lactose, magnesium stearate, methylparaben, polysorbate 80, propylparaben, sodium laurel sulfate

QUESTIONS OR COMMENTS

TAMPER EVIDENT: DO NOT USE IF IMPRINTED SAFETY SEAL UNDER CAP OR BAND AROUND ANY CAPSULE IS MISSING OR DAMAGED

Distributed by: Qualitest Pharmaceuticals, Inc.

DOSAGE & ADMINISTRATION

adults and children 12 years and over: take 1 to 2 capsules every 4-6 hours; not more than 6 doses in 24 hours
children under 12 years: ask a doctor